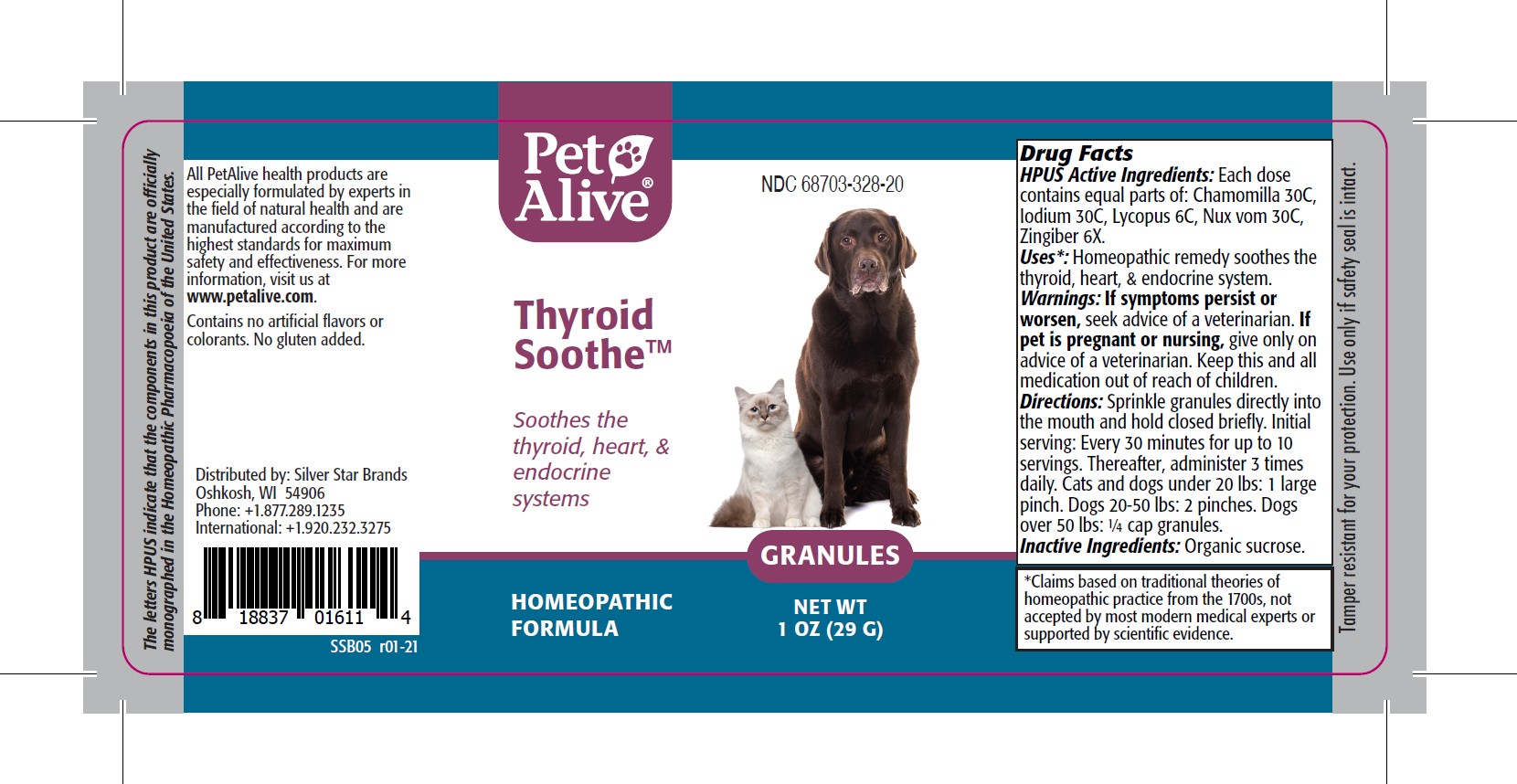 DRUG LABEL: PetAlive Thyroid Soothe
NDC: 68703-328 | Form: GRANULE
Manufacturer: SILVER STAR BRANDS
Category: homeopathic | Type: OTC ANIMAL DRUG LABEL
Date: 20251216

ACTIVE INGREDIENTS: MATRICARIA RECUTITA 30 [hp_C]/40 mg; IODINE 30 [hp_C]/40 mg; LYCOPUS VIRGINICUS 6 [hp_C]/40 mg; STRYCHNOS NUX-VOMICA SEED 30 [hp_C]/40 mg; GINGER 6 [hp_X]/40 mg
INACTIVE INGREDIENTS: SUCROSE

PetAlive Thyroid Soothe

PURPOSE

Soothes the thyroid, heart and endocrine systems

HPUS Active Ingredients:

Chamomilla 30C
lodium 30C
Lycopus 6C
Nux vom 30C
Zingiber 6X

INDICATIONS AND USAGE

Uses: Homeopathic remedy soothes the thyroid, heart and endocrine system.

WARNINGS

Warnings: If symptoms persist or worsen, seek advice of a veterinarian.

PREGNANCY OR BREAST FEEDING

If pet is pregnant or nursing, give only on advice of a veterinarian.

KEEP OUT OF REACH OF CHILDREN

Keep this and all medication out of reach of children.

DOSAGE AND ADMINISTRATION

Directions: Sprinkle granules directly into the mouth and hold closed briefly. Initial serving: Every 30 minutes for up to 10 servings. Thereafter, administer 3 times daily. Cats and dogs under 20 lbs: 1 large pinch. Dogs 20-50 lbs: 2 pinches. Dogs over 50 lbs: 1/4 cap granules.

Inactive Ingredients: Organic sucrose.

INFORMATION FOR OWNERS/CAREGIVERS

The letters HPUS indicate that the components in this product are officially monographed in the Homeopathic Pharmacopoeia of the United States.

All PetAlive health products are especially formulated by experts in the field of natural health and are manufactured according to the highest standards for maximum safety and effectiveness. For more information, visit us at www.petalive.com.

Contains no artificial flavors or colorants. No gluten added.

Distributed by: Silver Star Brands
Oshkosh, WI 54906
Phone: +1.877.289.1235
International: +1.920.232.3275

STORAGE AND HANDLING

Tamper resistant for your protection. Use only if safety seal is intact.